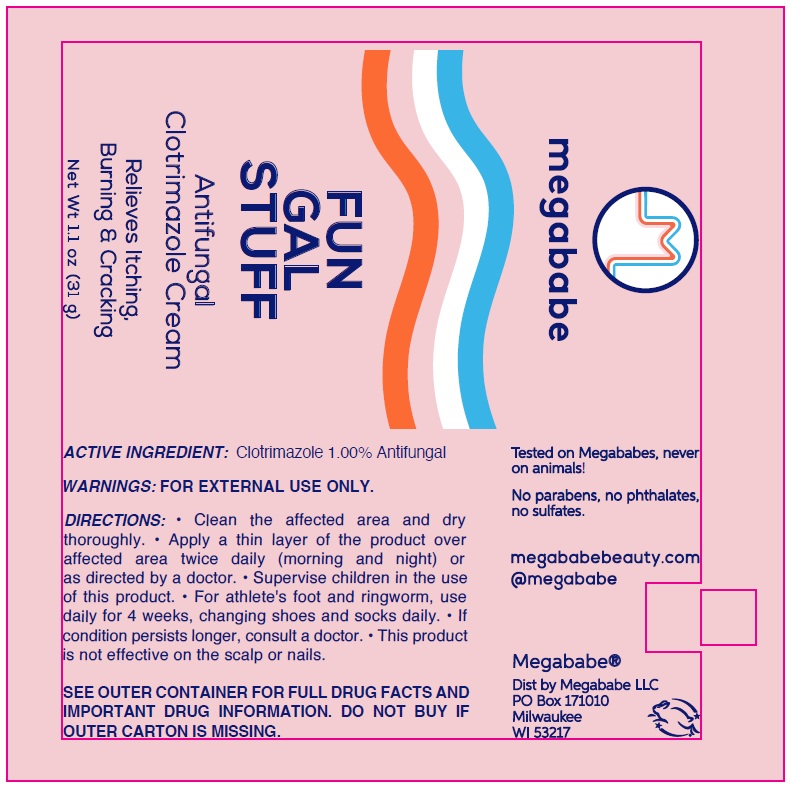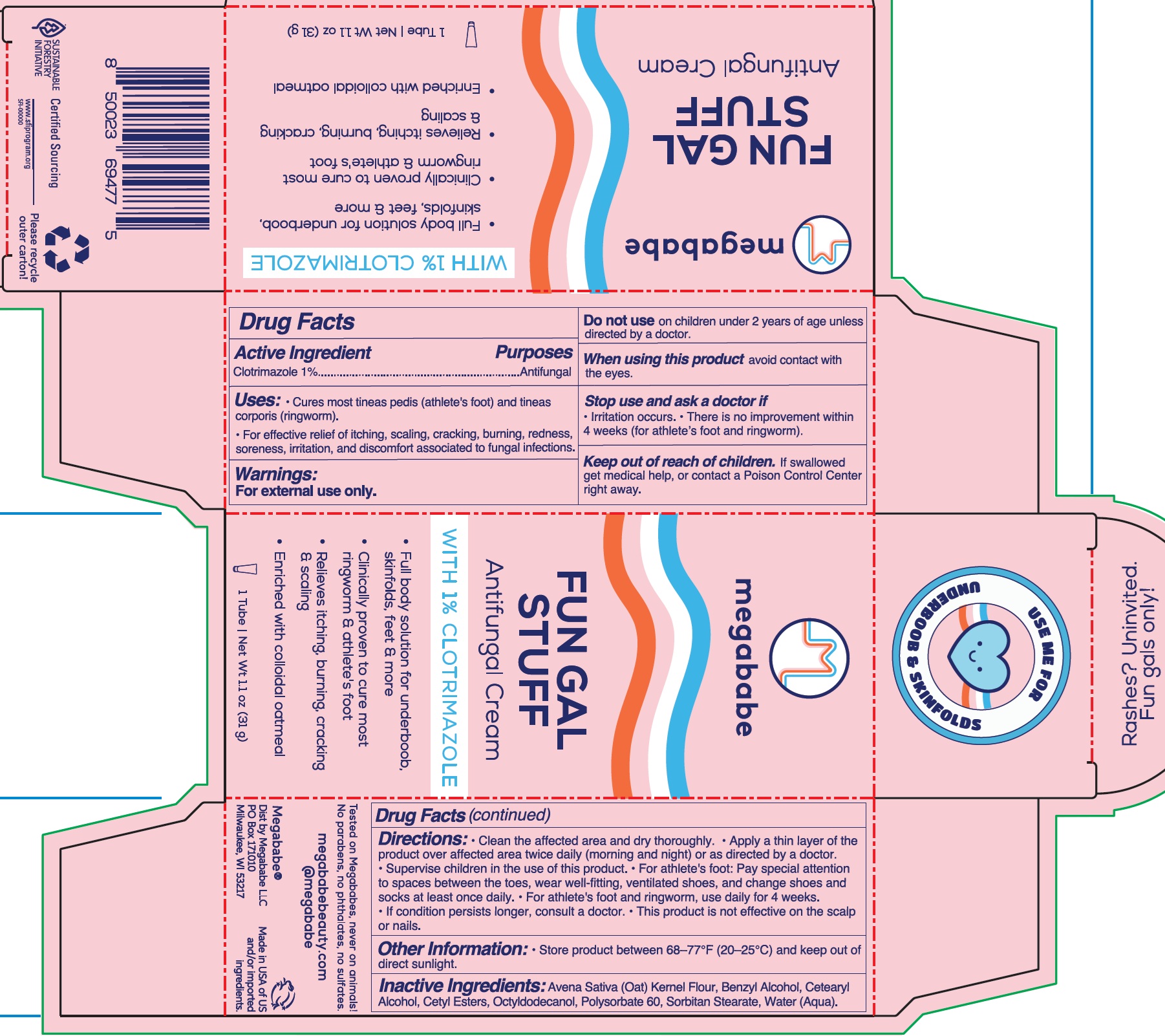 DRUG LABEL: Megababe Fun Gal Stuff Antifungal
NDC: 84000-908 | Form: CREAM
Manufacturer: Megababe LLC
Category: otc | Type: HUMAN OTC DRUG LABEL
Date: 20260225

ACTIVE INGREDIENTS: CLOTRIMAZOLE 10 mg/1 g
INACTIVE INGREDIENTS: OATMEAL; BENZYL ALCOHOL; CETOSTEARYL ALCOHOL; CETYL ESTERS WAX; OCTYLDODECANOL; POLYSORBATE 60; SORBITAN MONOSTEARATE; WATER

Megababe Fun Gal Stuff Antifungal Cream

Active Ingredient

Clotrimazole 1%

Purpose

Antifungal

Uses:

- Cures most tineas pedis (athlete's foot) and tineas corporis (ringworm).
- For effective relief of itching, scalling, cracking, burning, redness, soreness, irritation, and discomfort associated to fungal infections.

Warnings:

For external use only.

Do not use

on children under 2 years of age unless directed by a doctor.

When using this product

avoid contact with the eyes.

Stop use and ask a doctor if

- Irriation occurs
- There is no improvement within 4 weeks (for athlete's foot and ringworm).

Keep out of reach of children.

If swallowed get medical help, or contact a Posion Control Center right away.

Directions:

- Clean the affected area and dry thoroughly.
- Apply a thin layer of the product over affected area twice daily (morning and night) or as directed by a doctor.
- Supervise children in the use of this product.
- For athlete's foot: Pay special attention to spaces between the toes, wear well-fitting, ventilated shoes, and change shoes and socks at least once daily.
- For athlete's foot and ringworm, use daily for 4 weeks.
- If condition persists longer, consult a doctor.
- This product is not effective on the scalp or nails.

Other Information:

- Store product between 68—77°F (20—25°C) and keep out of direct sunlight.

Inactive Ingredients:

Avena Sativa (Oat) Kernel Flour, Benzyl Alcohol, Cetearyl Alcohol, Cetyl Esters, Octyldodecanol, Polysorbate 60, Sorbitan Stearate Water (Aqua).